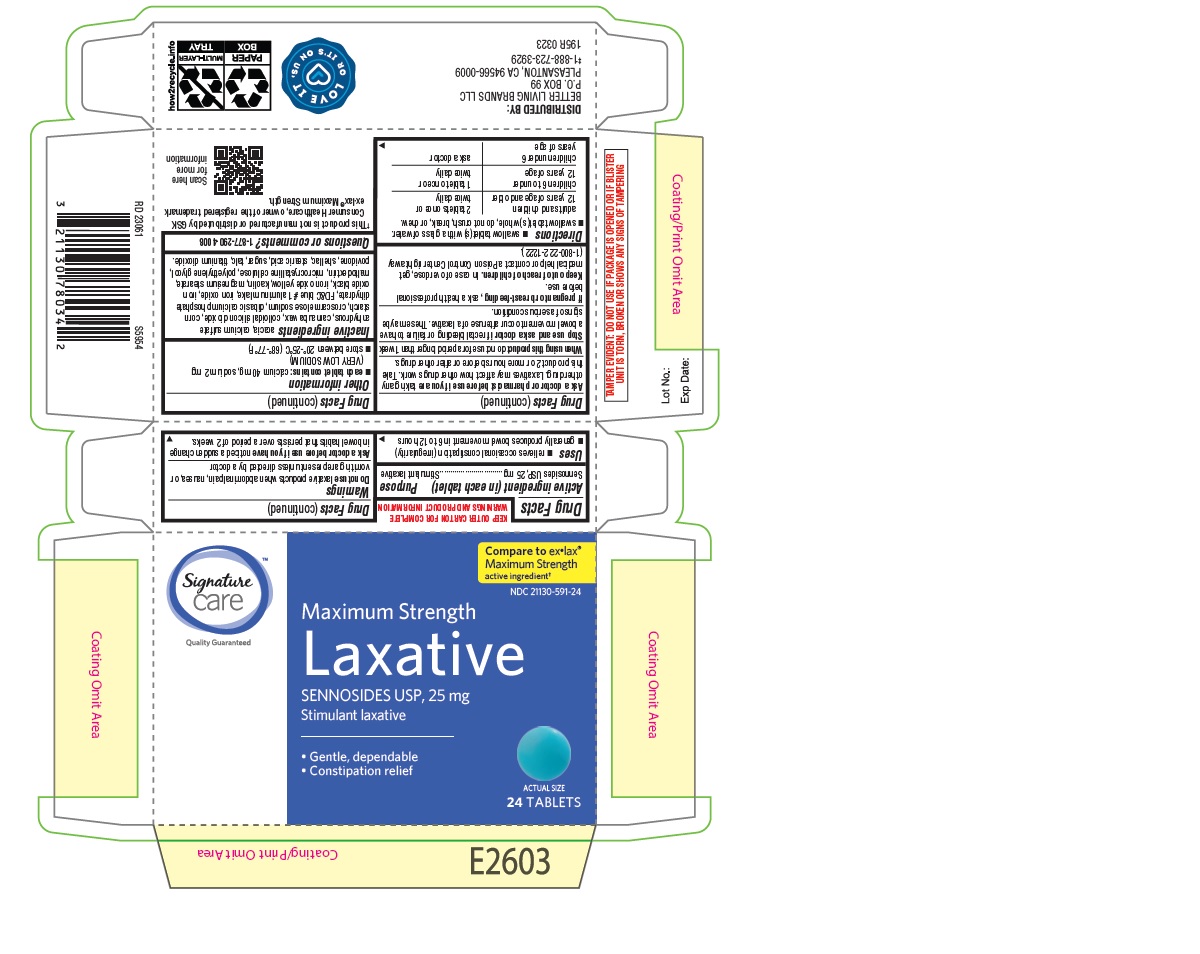 DRUG LABEL: Laxative
NDC: 21130-591 | Form: TABLET
Manufacturer: BETTER LIVING BRANDS LLC.
Category: otc | Type: HUMAN OTC DRUG LABEL
Date: 20250212

ACTIVE INGREDIENTS: SENNOSIDES 25 mg/1 1
INACTIVE INGREDIENTS: ACACIA; CROSCARMELLOSE SODIUM; POVIDONE; CALCIUM SULFATE ANHYDROUS; FD&C BLUE NO. 1 ALUMINUM LAKE; FERROSOFERRIC OXIDE; MICROCRYSTALLINE CELLULOSE; POLYETHYLENE GLYCOL, UNSPECIFIED; DIBASIC CALCIUM PHOSPHATE DIHYDRATE; TALC; STEARIC ACID; SUCROSE; STARCH, CORN; KAOLIN; SHELLAC; FERROUS OXIDE; FERRIC OXIDE YELLOW; MAGNESIUM STEARATE; MALTODEXTRIN; TITANIUM DIOXIDE; CARNAUBA WAX; SILICON DIOXIDE

195-Albertsons-Laxative Sennosides USP 25 mg Tablets

Active ingredient (in each tablet)

Sennosides USP, 25 mg

Purpose

Stimulant laxative

Uses

- relieves occasional constipation (irregularity)
- generally produces bowel movement in 6 to 12 hours

Warnings

Do not use laxative products when abdominal pain, nausea, or vomiting are present unless directed by a doctor

Ask a doctor before use if you have noticed a sudden change in bowel habits that persists over a period of 2 weeks.

Ask a doctor or pharmacist before use if you are taking any other drug. Laxatives may affect how other drugs work. Take this product 2 or more hours before or after other drugs.

When using this product do not use for a period longer than 1 week

Stop use and ask a doctor if rectal bleeding or failure to have a bowel movement occur after use of a laxative. These may be signs of a serious condition.

PREGNANCY OR BREAST FEEDING

If pregnant or breast-feeding, ask a health professional before use.

Keep out of reach of children. In case of overdose, get medical help or contact a Poison Control Center right away (1-800-222-1222).

Directions

- swallow tablet (s) with a glass of water.
- swallow tablet (s) whole, do not crush, break or chew.

adults and children 12 years of age and older | 2 tablets once or twice daily
children 6 to under 12 years of age | 1 tablet once or twice daily
children under 6 years of age | ask a doctor

Other information

- each tablet contains: calcium 40 mg, sodium 2 mg (VERY LOW SODIUM)
- store between 20°-25°C (68°-77°F)

INACTIVE INGREDIENT

Inactive ingredients acacia, calcium sulfate anhydrous, carnauba wax, colloidal silicon dioxide, corn starch, croscarmellose sodium, dibasic calcium phosphate dihydrate, FD&C blue #1 aluminum lake, iron oxide, iron oxide black, iron oxide yellow, kaolin, magnesium stearate, maltodextrin, microcrystalline cellulose, polyethylene glycol, povidone, shellac, stearic acid, sugar, talc, titanium dioxide.

Questions or comments?1-877-290-4008